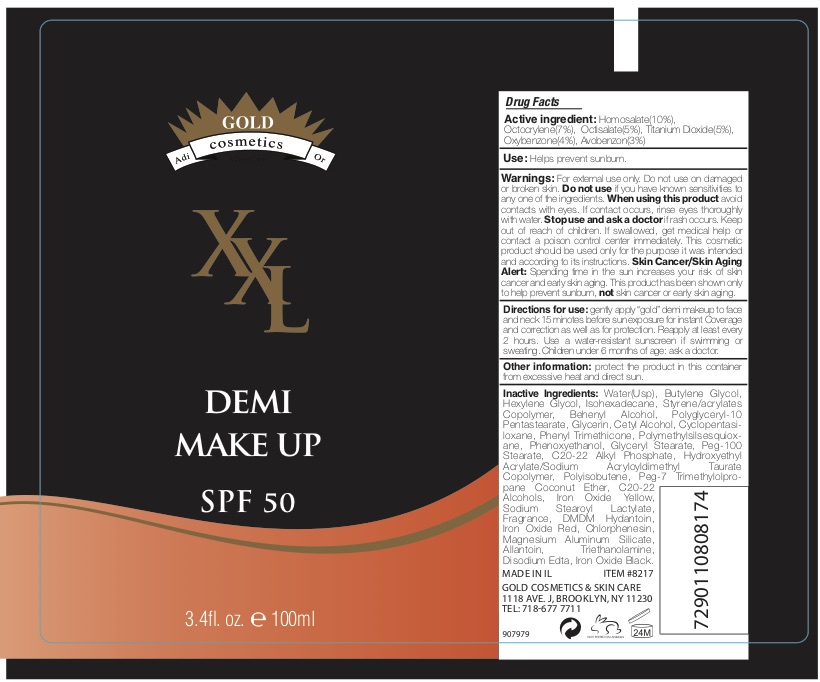 DRUG LABEL: XXL Demi Make Up SPF 50
NDC: 69435-1906 | Form: CREAM
Manufacturer: Peer Pharma Ltd.
Category: otc | Type: HUMAN OTC DRUG LABEL
Date: 20190906

ACTIVE INGREDIENTS: OCTOCRYLENE 4 g/100 mL; OCTISALATE 5 g/100 mL; AVOBENZONE 3 g/100 mL; HOMOSALATE 13 g/100 mL; OXYBENZONE 7 g/100 mL
INACTIVE INGREDIENTS: JOJOBA OIL; PHENOXYETHANOL; GLYCERYL MONOSTEARATE; ETHYLHEXYLGLYCERIN; ALMOND OIL; DMDM HYDANTOIN; ALLANTOIN; CHLORPHENESIN; HYALURONATE SODIUM; ASCORBYL TETRAISOPALMITATE; ISOHEXADECANE; CETOSTEARYL ALCOHOL; CETEARYL GLUCOSIDE; CYCLOMETHICONE 5; GLYCERIN; PUNICA GRANATUM ROOT BARK; SHEA BUTTER; POTASSIUM CETYL PHOSPHATE; NIACINAMIDE; DIMETHICONE; SEA SALT; ALOE VERA LEAF; VITAMIN A PALMITATE; .ALPHA.-TOCOPHEROL ACETATE; PANTHENOL; GREEN TEA LEAF; CHAMAEMELUM NOBILE FLOWER; AVOCADO OIL; WATER; DIETHYLAMINO HYDROXYBENZOYL HEXYL BENZOATE

Gold Cosmetics Demi Make Up SPF 50

PACKAGE LABEL

ACTIVE INGREDIENT

Oxybenzone 7%

Octocrylene 4%

Octisalate 5%

Avobenzone 3%

Homosalate 13%

Keep out of reach of children.

PURPOSE

Provides SPF 50 protection

INDICATIONS AND USAGE

Directions for Use: Apply generously to face and body regularly before sun exposure and as needed.

Reapply: after 40 minutes before of or 80 minutes of swimming or sweating, immediately after towel drying, and at least every 2 hours.

DOSAGE AND ADMINISTRATION

Directions for Use: Apply generously to face and body regularly before sun exposure and as needed.

Reapply: after 40 minutes before of or 80 minutes of swimming or sweating, immediately after towel drying, and at least every 2 hours.